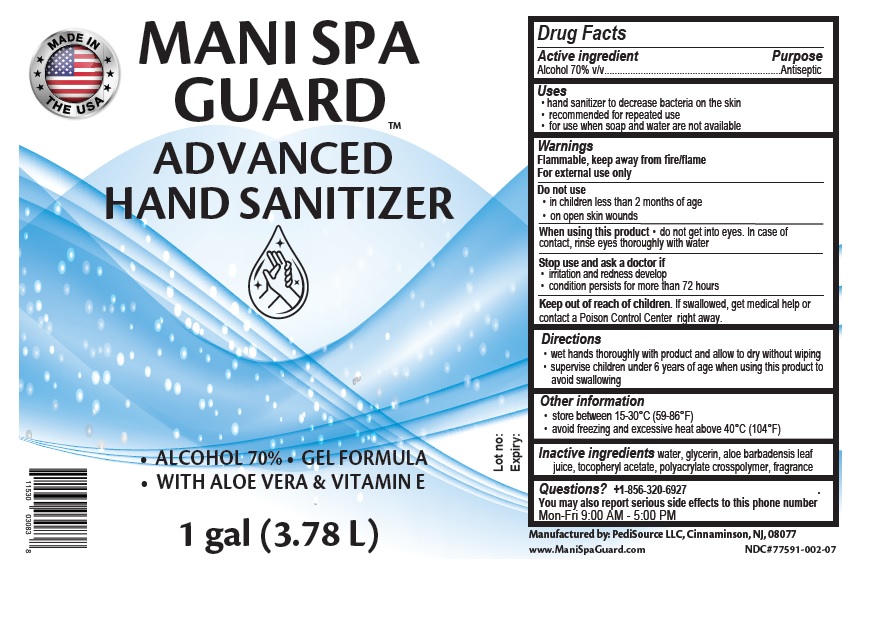 DRUG LABEL: MANI SPA GUARD ADVANCED HAND SANITIZER
NDC: 77591-002 | Form: GEL
Manufacturer: Pedisource
Category: otc | Type: HUMAN OTC DRUG LABEL
Date: 20200528

ACTIVE INGREDIENTS: ALCOHOL 70 mL/100 mL
INACTIVE INGREDIENTS: WATER; GLYCERIN; ALOE VERA LEAF; .ALPHA.-TOCOPHEROL ACETATE; AMMONIUM ACRYLOYLDIMETHYLTAURATE, DIMETHYLACRYLAMIDE, LAURYL METHACRYLATE AND LAURETH-4 METHACRYLATE COPOLYMER, TRIMETHYLOLPROPANE TRIACRYLATE CROSSLINKED (45000 MPA.S)

MANI SPA GUARDTM ADVANCED HAND SANITIZER

Active ingredient

Alcohol 70% v/v

Purpose

Antiseptic

Uses

• hand sanitizer to decrease bacteria on the skin
• recommended for repeated use
• for use when soap and water are not available

Warnings

Flammable, keep away from fire/flame
For external use only

Do not use• in children less than 2 months of age
• on open skin wounds

When using this product • do not get into eyes. In case of
contact, rinse eyes thoroughly with water

Stop use and ask a doctor if
• irritation and redness develop
• condition persists for more than 72 hours

Keep out of reach of children. If swallowed, get medical help or contact a Poison Control Center right away.

Directions

• wet hands thoroughly with product and allow to dry without wiping
• supervise children under 6 years of age when using this product to avoid swallowing

Other information

• store between 15-30°C (59-86°F)
• avoid freezing and excessive heat above 40°C (104°F)

Inactive ingredients

water, glycerin, aloe barbadensis leaf juice, tocopheryl acetate, polyacrylate crosspolymer, fragrance

Questions?

+1-856-320-6927
You may also report serious side effects to this phone number.
Mon-Fri 9:00 AM - 5:00 PM

MADE IN * * * THE USA

• ALCOHOL 70% • GEL FORMULA

• WITH ALOE VERA & VITAMIN E

Manufactured by: PediSource LLC, Cinnaminson, NJ, 08077
www.ManiSpaGuard.co m